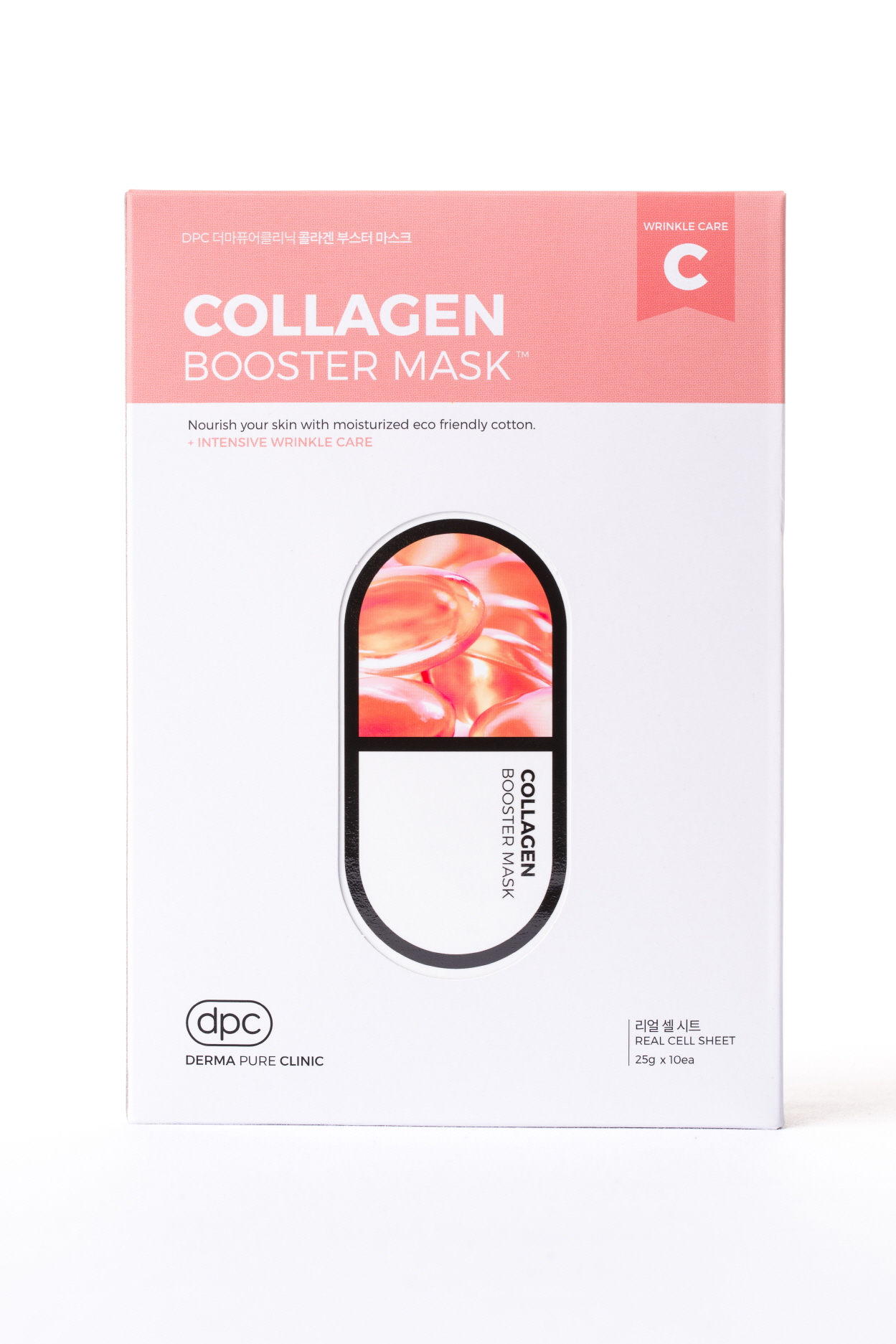 DRUG LABEL: DPC COLLAGEN BOOSTER MASK
NDC: 71673-0002 | Form: LIQUID
Manufacturer: MSCO
Category: otc | Type: HUMAN OTC DRUG LABEL
Date: 20170823

ACTIVE INGREDIENTS: ADENOSINE 0.04 g/100 g
INACTIVE INGREDIENTS: WATER; HYALURONATE SODIUM; GLYCERIN

Drug Facts

ACTIVE INGREDIENT

ADENOSINE

INACTIVE INGREDIENT

Water
Propanediol
Glycerin
Erythritol
Butylene Glycol
Caprylic/Capric Triglyceride
Dipotassium Glycyrrhizate
Disodium EDTA
Carbomer
Xanthan Gum
Hydroxyethylcellulose
Chlorphenesin
Sodium Hyaluronate
Squalane
Hydrolyzed Collagen
Simmondsia Chinensis (Jojoba) Seed Oil
Glycine Soja (Soybean) Seed Extract
Phaseolus radiatus seed extract
Thioctic Acid
Glutathione
Polyglutamic Acid
Methylpropanediol
Phenoxyethanol
Polyacrylate-13
Polyisobutene
Polysorbate 20
Sorbitan isostearate
Glyceryl Stearate
Polysorbate 60
Arginine
Citrus Grandis (Grapefruit) Seed Extract
Acorus Calamus Root Extract
Perilla Ocymoides Leaf Extract
1,2-Hexanediol
Caprylyl Glycol
Glycyrrhiza Glabra (Licorice) Root Extract
Zingiber Officinale (Ginger) Root Extract
Schizandra Chinensis Fruit Extract
Coptis Japonica Root Extract
Camellia Sinensis Leaf Extract
Fragrance

PURPOSE

Skin Protectant - Anti wrinkle

keep out of reach of the children

INDICATIONS AND USAGE

1. After cleansing wipe water and apply skin lotion on face.
2. Apply the mask evenly over the face for 10-20 minutes and remove.
3. Pad the left over residue lightly to absorb.

WARNINGS

For external use only.
Avoid contact with eyes. Not for human consumption.
Discontinue use if irritation occurs.
If irritation persists, consult a physician.

DOSAGE AND ADMINISTRATION

for external use only